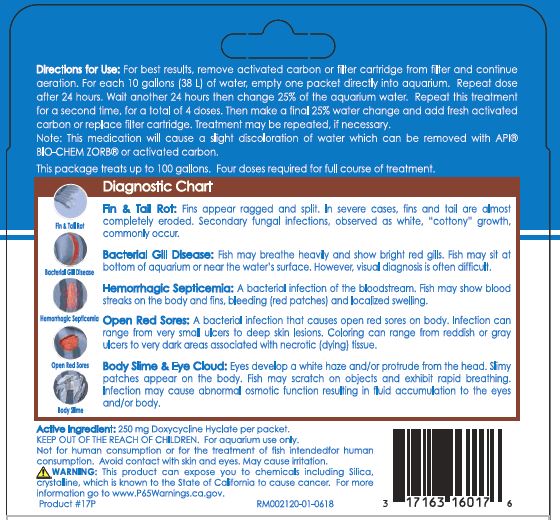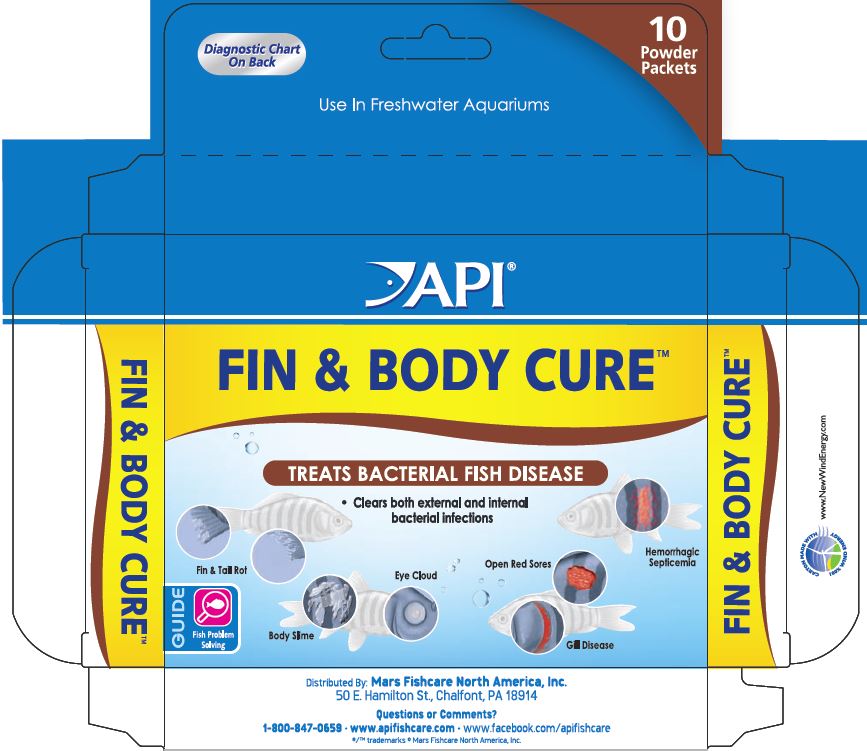 DRUG LABEL: API FIN and BODY CURE
NDC: 17163-017 | Form: POWDER
Manufacturer: MARS FISHCARE NORTH AMERICA, INC.
Category: animal | Type: OTC ANIMAL DRUG LABEL
Date: 20211229

ACTIVE INGREDIENTS: DOXYCYCLINE HYCLATE 250 mg/2 g

Drug Label

Active Ingredient: 250 mg Doxycycline Hyclate per packet.

DOSAGE AND ADMINISTRATION

Directions for Use:

For best results, remove activated carbon or filter cartridge from filter and continue aeration.

For each 10 gallons (38 L) of water, empty one packet directly into aquarium.

Repeat dose after 24 hours. Wait another 24 hours then change 25% of the aquarium water.

Repeat this treatment for a second time, for a total of 4 doses.

Then make a final 25% water change and add fresh activated carbon or replace filter cartridge.

Treatment may be repeated, if necessary.

Note: This medication will cause a slight discoloration of water which can be removed with API BIO-CHEM ZORB or activated carbon

This package treats up to 100 gallons.

Four doses required for full course of treatment.

INDICATIONS AND USAGE

Diagnostic Chart

Fin and Tail Rot:

Fins appear ragged and split. In severe cases, fins and tail are almost completely eroded. Secondary fungal infections, observed as white, "cottony" growth, commonly occur.

Bacterial Gill Disease:

Fish may breathe heavily and show bright red gills. Fish may sit at bottom of aquarium or near the water's surface. However, visual diagnosis is often difficult.

Hemorrhagic Septicemia:

A bacterial infection of the bloodstream. Fish may show blood streaks on the body and fins, bleeding (red patches) and localized swelling.

Open Red Sores:

A bacterial infection that causes open red sores on body. Infection can range from very small ulcers to deep skin lesions. Coloring can range from reddish or gray ulcers to very dark areas associated with necrotic (dying) tissue.

Body Slime and Eye Cloud:

Eyes develop a white haze and/or protrude from the head. Slimy patches appear on the body. Fish may scratch on objects and exhibit rapid breathing. Infection may cause abmormal osmotic funstion resulting in fluid accumulation to the eyes and/or body.

WARNINGS AND PRECAUTIONS

KEEP OUT OF THE REACH OF CHILDREN.

For aquarium use only.

Not for human consumption or for the treatment of fish intended for human consumption.

Avoid contact with skin and eyes.

May cause irritation.

! WARNING:

This product can expose you to chemicals including Silica, crystalline, which is known to the State of California to cause cancer.

For more information go to www.P65Warnings.ca.gov.

PACKAGE LABEL

Diagnostic Chart

On Back

10

Powdered

Packets

API

FIN and BODY CURE

TREATS BACTERIAL FISH DISEASE

Clears both external and internal bacterial infections

Fin and Tail Rot

Eye Cloud

Open Red Sores

Hemorrhagic Septicemia

Body Slime

Gill Disease

GUIDE

Fish Problem

Solving